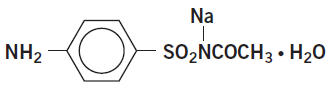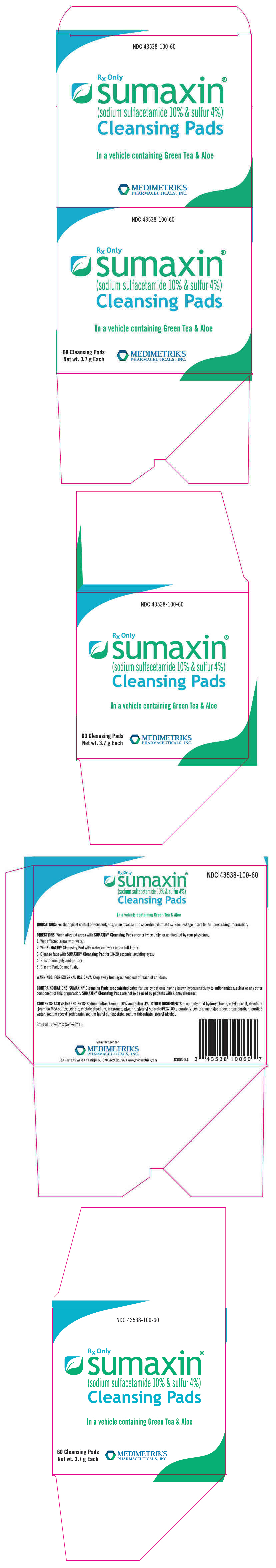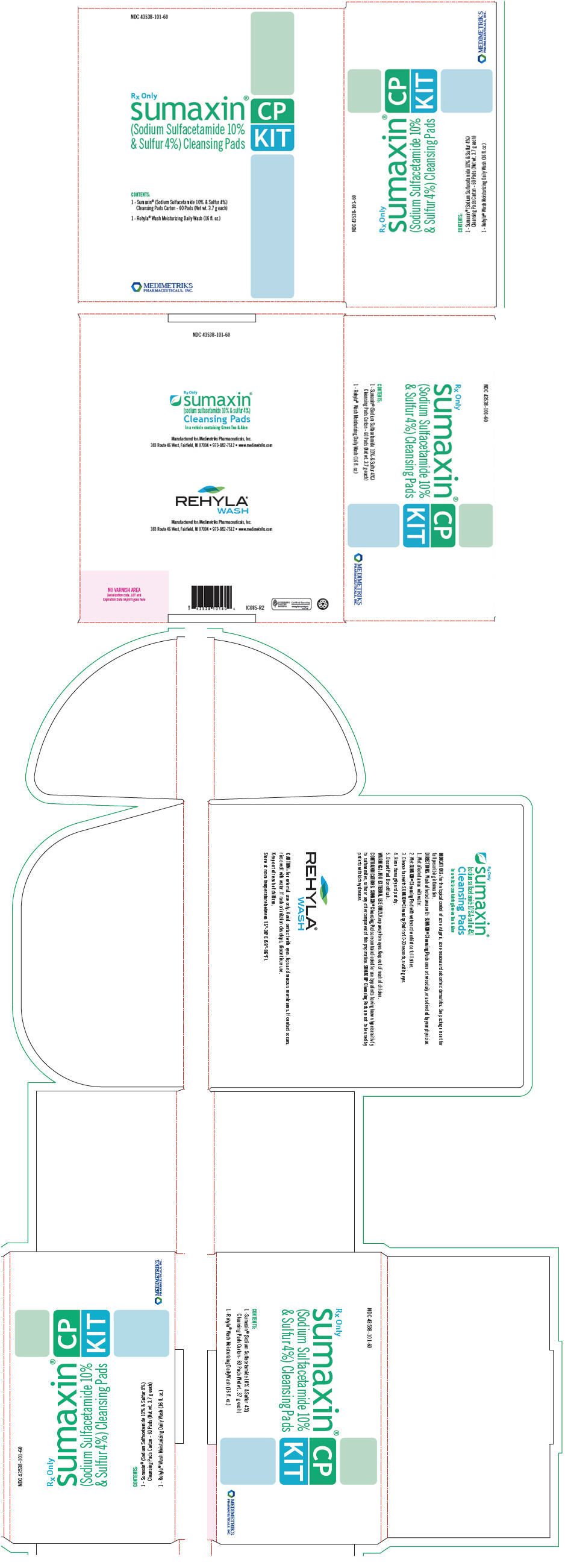 DRUG LABEL: Sumaxin 
NDC: 43538-100 | Form: CLOTH
Manufacturer: Medimetriks Pharmaceuticals, Inc.
Category: prescription | Type: HUMAN PRESCRIPTION DRUG LABEL
Date: 20231215

ACTIVE INGREDIENTS: Sulfacetamide sodium 100 mg/1 g; Sulfur 40 mg/1 g
INACTIVE INGREDIENTS: aloe; butylated hydroxytoluene; cetyl alcohol; disodium oleamido monoethanolamine sulfosuccinate; edetate disodium; glycerin; green tea leaf; methylparaben; propylparaben; water; sodium cocoyl isethionate; sodium lauryl sulfoacetate; sodium thiosulfate; stearyl alcohol

sumaxin®
(sodium sulfacetamide 10% & sulfur 4%)
Cleansing Pads

In a vehicle containing Green Tea & Aloe

Rx Only

DESCRIPTION

Sodium sulfacetamide is a sulfonamide with antibacterial activity while sulfur acts as a keratolytic agent. Chemically sodium sulfacetamide is N-[(4-aminophenyl) sulfonyl]-acetamide, monosodium salt, monohydrate. The structural formula is:

Each pad of Sumaxin® (sodium sulfacetamide 10% & sulfur 4%) Cleansing Pads is coated with a cleanser-based formulation. Each gram of this cleanser-based formulation contains 100 mg of Sodium Sulfacetamide and 40 mg of Sulfur. The cleanser base consists of: aloe, butylated hydroxytoluene, cetyl alcohol, disodium oleamido MEA sulfosuccinate, edetate disodium, fragrance, glycerin, glyceryl stearate/PEG-100 stearate, green tea, methylparaben, propylparaben, purified water, sodium cocoyl isethionate, sodium lauryl sulfoacetate, sodium thiosulfate, stearyl alcohol.

CLINICAL PHARMACOLOGY

The most widely accepted mechanism of action of sulfonamides is the Woods-Fildes theory, which is based on the fact that sulfonamides act as competitive antagonists to para-aminobenzoic acid (PABA), an essential component for bacterial growth. While absorption through intact skin has not been determined, sodium sulfacetamide is readily absorbed from the gastrointestinal tract when taken orally and excreted in the urine, largely unchanged. The biological half-life has variously been reported as 7 to 12.8 hours. The exact mode of action of sulfur in the treatment of acne is unknown, but it has been reported that it inhibits the growth of Propionibacterium acnes and the formation of free fatty acids.

INDICATIONS

Sumaxin® (sodium sulfacetamide 10% & sulfur 4%) Cleansing Pads are indicated in the topical control of acne vulgaris, acne rosacea and seborrheic dermatitis.

CONTRAINDICATIONS

Sumaxin® (sodium sulfacetamide 10% & sulfur 4%) Cleansing Pads are contraindicated for use by patients having known hypersensitivity to sulfonamides, sulfur or any other component of this preparation. Sumaxin® (sodium sulfacetamide 10% & sulfur 4%) Cleansing Pads are not to be used by patients with kidney disease.

WARNINGS

Although rare, sensitivity to sodium sulfacetamide may occur. Therefore, caution and careful supervision should be observed when prescribing this drug for patients who may be prone to hypersensitivity to topical sulfonamides. Systemic toxic reactions such as agranulocytosis, acute hemolytic anemia, purpura hemorrhagica, drug fever, jaundice, and contact dermatitis indicate hypersensitivity to sulfonamides. Particular caution should be employed if areas of denuded or abraded skin are involved.

FOR EXTERNAL USE ONLY. Keep away from eyes. Keep out of reach of children. Keep container tightly closed.

PRECAUTIONS

General

If irritation develops, use of the product should be discontinued and appropriate therapy instituted. Patients should be carefully observed for possible local irritation or sensitization during long-term therapy. The object of this therapy is to achieve desquamation without irritation, but sodium sulfacetamide and sulfur can cause reddening and scaling of the epidermis. These side effects are not unusual in the treatment of acne vulgaris, but patients should be cautioned about the possibility.

Information for Patients

Avoid contact with eyes, eyelids, lips and mucous membranes. If accidental contact occurs, rinse with water. If excessive irritation develops, discontinue use and consult your physician.

Carcinogenesis, Mutagenesis and Impairment of Fertility

Long-term studies in animals have not been performed to evaluate carcinogenic potential.

PREGNANCY

Category C

Animal reproduction studies have not been conducted with Sumaxin® (sodium sulfacetamide 10% & sulfur 4%) Cleansing Pads. It is also not known whether Sumaxin® (sodium sulfacetamide 10% & sulfur 4%) Cleansing Pads can cause fetal harm when administered to a pregnant woman or can affect reproduction capacity. Sumaxin® (sodium sulfacetamide 10% & sulfur 4%) Cleansing Pads should be given to a pregnant woman only if clearly needed.

NURSING MOTHERS

It is not known whether sodium sulfacetamide is excreted in the human milk following topical use of Sumaxin® (sodium sulfacetamide 10% & sulfur 4%) Cleansing Pads. However, small amounts of orally administered sulfonamides have been reported to be eliminated in human milk. In view of this and because many drugs are excreted in human milk, caution should be exercised when Sumaxin® (sodium sulfacetamide 10% & sulfur 4%) Cleansing Pads are administered to a nursing woman.

PEDIATRIC USE

Safety and effectiveness in children under the age of 12 have not been established.

ADVERSE REACTIONS

Although rare, sodium sulfacetamide may cause local irritation.

DOSAGE AND ADMINISTRATION

Wash affected area(s) with cleansing pad once or twice daily, or as directed by your physician. Wet area(s) with water. Wet pad with a little water and work into a full lather. Cleanse area(s) with pad for 10-20 seconds, avoiding eyes. Rinse thoroughly and pat dry. Discard pad. Do not flush.

HOW SUPPLIED

Sumaxin® (sodium sulfacetamide 10% & sulfur 4%) Cleansing Pads are available in boxes of 60 cloths (3.7 g), NDC 43538-100-60.

STORAGE AND HANDLING

Store at 15°-30° C (59°-86° F).

To report SUSPECTED ADVERSE REACTIONS, contact Medimetriks Pharmaceuticals, Inc., at 1-973-882-7512 or FDA at 1-800-FDA-1088 or www.fda.gov/medwatch.

Manufactured for:
MEDIMETRIKS
PHARMACEUTICALS, INC.

383 Route 46 West
Fairfield, NJ 07004-2402 USA

www.medimetriks.com

IP001-R5
Rev. 10/17

PRINCIPAL DISPLAY PANEL - 60 Pad Carton

NDC 43538-100-60

Rx Only
sumaxin®
(sodium sulfacetamide 10% & sulfur 4%)
Cleansing Pads

In a vehicle containing Green Tea & Aloe

60 Cleansing Pads
Net wt. 3.7 g Each

MEDIMETRIKS
PHARMACEUTICALS, INC.

PRINCIPAL DISPLAY PANEL - Kit Carton

NDC 43538-101-60

Rx Only
sumaxin®
(Sodium Sulfacetamide 10%
& Sulfur 4%) Cleansing Pads
CP
KIT

CONTENTS:

1 - Sumaxin® (Sodium Sulfacemide 10% & Sulfur 4%)
  Cleansing Pads Carton - 60 Pads (Net wt. 3.7 g each)
1 - Rehyla® Wash Moisturizing Daily Wash (16 fl. oz.)

MEDIMETRIKS
PHARMACEUTICALS, INC.